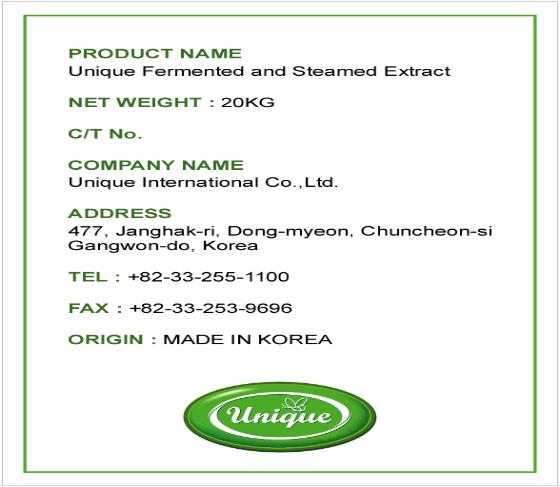 DRUG LABEL: DANCHUN JADE oriental herb cosmetics 
NDC: 50025-1001 | Form: LIQUID
Manufacturer: UniqueInternational Co, Ltd
Category: otc | Type: HUMAN OTC DRUG LABEL
Date: 20091109

ACTIVE INGREDIENTS: GLYCERIN 1 kg/20 kg

ACTIVE INGREDIENT

INGREDIENTS:

Houttuynia Cordata Thunb, Angelica gigas Nakai, Artemisia princeps var, orientalis HARA, Cnidium officinale Makino(Ginger), Sophora japonica L, Mentha arvensis L, Prunus armeniaca, Lonicera japonica Thunb, Zingiber officinale Rosroe, Scrophularia buergeriana Miq, Camella Sinensis L, Argemisia princeps pamp, Calendula officinalis L, Platycodon grandiflorum (Jacq.) A.DC, Water, Glycerin

WARNING:

1. Containing medicinal herbs extract and natural herb oils as olive oil, camellia oil, grape seed oil, coconut oil, palm oil, etc.

2. By special aging technology, it is free from dermatic trouble even for extremely sensitive skin.

3. Not only providing various nutrients into the skin, but also removing waste materials from the skin.

4. Protecting skin layer from dehydration and defensive natural system of the skin with natural moisturizing ingredients.

WHEN USING

DIRECTION OF USE:

1. After spraying the skin on the troubled part enough to make it slip down, rub with your palms so that the essence skin can be absorbed well

2. Use 4-5 occasions daily. Make sure to use this product before going to bed

3. To prevent secondary infection during sleep